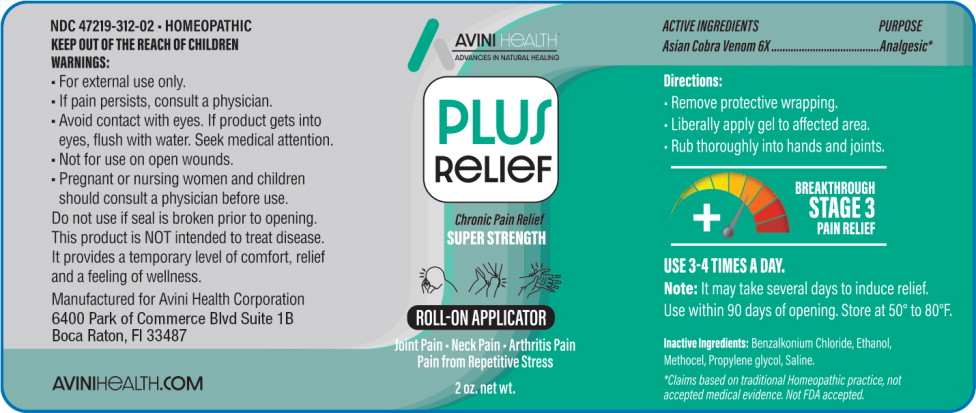 DRUG LABEL: Plus Relief
NDC: 47219-312 | Form: GEL
Manufacturer: Nutra Pharma Corporation
Category: homeopathic | Type: HUMAN OTC DRUG LABEL
Date: 20251104

ACTIVE INGREDIENTS: NAJA NAJA VENOM 6 [hp_X]/1 mL
INACTIVE INGREDIENTS: BENZALKONIUM CHLORIDE; ALCOHOL; CARBOXYMETHYLCELLULOSE SODIUM, UNSPECIFIED; PROPYLENE GLYCOL; ISOTONIC SODIUM CHLORIDE SOLUTION

Drug Facts

ACTIVE INGREDIENTS

Asian Cobra Venom 6X

PURPOSE

Analgesic*

*Claims based on traditional Homeopathic practice not accepted medical evidence. Not FDA accepted.

Directions:

- Remove protective wrapping.
- Liberally apply gel to affected area.
- Rub thoroughly into hands and joints.

INDICATIONS AND USAGE

USE 3-4 TIMES A DAY.

Note:It may take several days to induce relief. Use within 90 days of opening. Store at 50° to 80°F.

Inactive Ingredients:

Benzalkonium Chloride, Ethanol, Methocel, Propylene glycol, Saline.

NDC 47219-312-02■ HOMEOPATHIC

WARNINGS:

- For external use only.
- If pain persists, consult a physician.
- Avoid contact with eyes. If product gets into eyes, flush with water. Seek medical attention.
- Not for use on open wounds.

PREGNANCY

- Pregnant or nursing women and children should consult a physician before use.

Do not use if seal is broken prior to opening.

This product is NOT intended to treat disease. It provides a temporary level of comfort, relief and a feeling of wellness.

Principal Display Panel - 2 oz Bottle Label

AVINIHEALTH ™
ADVANCES IN NATURAL HEALING

PLUS
RELIEF

Chronic Pain Relief

SUPER STRENGTH

ROLL-ON APPLICATOR

Joint Pain ■ Neck Pain ■ Arthritis Pain
Pain from Repetitive Stress

2 oz. net wt.